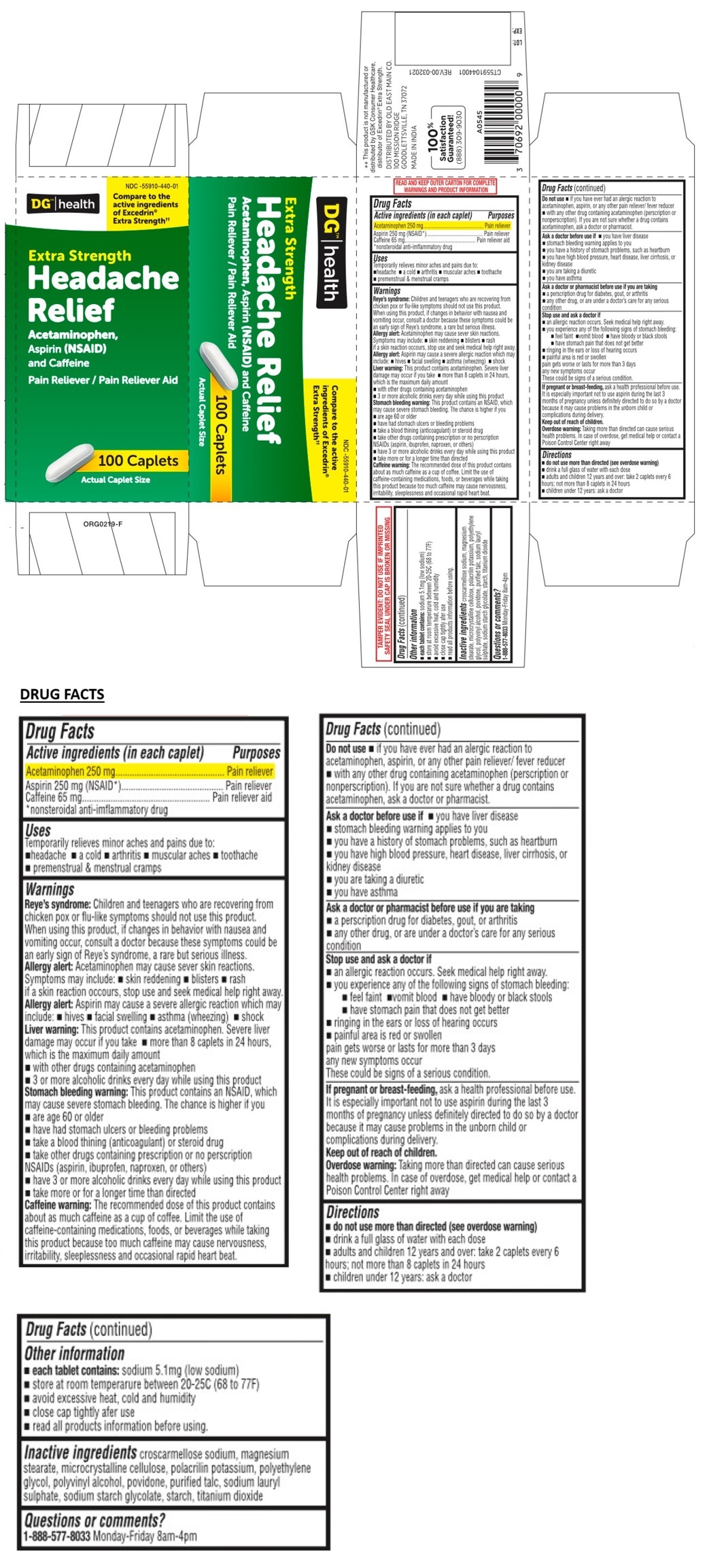 DRUG LABEL: Extra Strength Headache Relief
NDC: 55910-440 | Form: TABLET, COATED
Manufacturer: Dollar General
Category: otc | Type: HUMAN OTC DRUG LABEL
Date: 20241231

ACTIVE INGREDIENTS: ACETAMINOPHEN 250 mg/1 1; ASPIRIN 250 mg/1 1; CAFFEINE 65 mg/1 1
INACTIVE INGREDIENTS: CROSCARMELLOSE SODIUM; MAGNESIUM STEARATE; MICROCRYSTALLINE CELLULOSE; POLACRILIN POTASSIUM; POLYETHYLENE GLYCOL, UNSPECIFIED; POLYVINYL ALCOHOL, UNSPECIFIED; POVIDONE, UNSPECIFIED; TALC; SODIUM LAURYL SULFATE; SODIUM STARCH GLYCOLATE TYPE A; STARCH, CORN; TITANIUM DIOXIDE

Extra Strength Headache Relief

Active ingredients (in each caplet)

Acetaminophen 250 mg
Aspirin 250 mg (NSAID*)
Caffeine 65 mg

*nonsteroidal anti-inflammatory drug

Purposes

Pain reliever
Pain reliever
Pain reliever aid

Uses

Temporarily relieves minor aches and pains due to:
• headache • a cold • arthritis • muscular aches • toothache • premenstrual & menstrual cramps

Warnings

Reye's syndrome: Children and teenagers who are recovering from chicken pox or flu-like symptoms should not use this product. When using this product, if changes in behavior with nausea and vomiting occur, consult a doctor because these symptoms could be an early sign of Reye's syndrome, a rare but serious illness.

Allergy alert: Acetaminophen may cause sever skin reactions.
Symptoms may include: • skin reddening • blisters • rash
if a skin reaction occurs, stop use and seek medical help right away.

Allergy alert: Aspirin may cause a severe allergic reaction which may include: • hives • facial swelling • asthma (wheezing) • shock

Liver warning: This product contains acetaminophen. Severe liver damage may occur if you take • more than 8 caplets in 24 hours, which is the maximum daily amount
• with other drugs containing acetaminophen
• 3 or more alcoholic drinks every day while using this product

Stomach bleeding warning: This product contains an NSAID, which may cause severe stomach bleeding. The chance is higher if you
• are age 60 or older
• have had stomach ulcers or bleeding problems
• take a blood thinning (anticoagulant) or steroid drug
• take other drugs containing prescription or no prescription NSAIDs (aspirin, ibuprofen, naproxen, or others)
• have 3 or more alcoholic drinks every day while using this product
• take more or for a longer time than directed

Caffeine warning: The recommended dose of this product contains about as much caffeine as a cup of coffee. Limit the use of caffeine-containing medications, foods, or beverages while taking this product because too much caffeine may cause nervousness, irritability, sleeplessness and occasional rapid heart beat.

Do not use • if you have ever had an allergic reaction to acetaminophen, aspirin, or any other pain reliever/ fever reducer
• with any other drug containing acetaminophen (prescription or nonprescription). If you are not sure whether a drug contains acetaminophen, ask a doctor or pharmacist.

Ask a doctor before use if • you have liver disease
• stomach bleeding warning applies to you
• you have a history of stomach problems, such as heartburn
• you have high blood pressure, heart disease, liver cirrhosis, or kidney disease
• you are taking a diuretic
• you have asthma

Ask a doctor or pharmacist before use if you are taking
• a prescription drug for diabetes, gout, or arthritis
• any other drug, or are under a doctor's care for any serious condition

Stop use and ask a doctor if
• an allergic reaction occurs. Seek medical help right away.
• you experience any of the following signs of stomach bleeding:
• feel faint • vomit blood • have bloody or black stools • have stomach pain that does not get better
• ringing in the ears or loss of hearing occurs
• painful area is red or swollen
pain gets worse or lasts for more than 3 days
any new symptoms occur
These could be signs of a serious condition.

If pregnant or breast-feeding, ask a health professional before use.
It is especially important not to use aspirin during the last 3 months of pregnancy unless definitely directed to do so by a doctor because it may cause problems in the unborn child or complications during delivery.

Keep out of reach of children.
Overdose warning: Taking more than directed can cause serious health problems. In case of overdose, get medical help or contact a Poison Control Center right away

Directions

• do not use more than directed (see overdose warning)
• drink a full glass of water with each dose
• adults and children 12 years and over: take 2 caplets every 6 hours; not more than 8 caplets in 24 hours
• children under 12 years: ask a doctor

Other information

• each tablet contains: sodium 5.1mg (low sodium)
• store at room temperature between 20-25C (68 to 77F)
• avoid excessive heat, cold and humidity
• close cap tightly after use
• read all products information before using.

Inactive ingredients

croscarmellose sodium, magnesium stearate, microcrystalline cellulose, polacrilin potassium, polyethylene glycol, polyvinyl alcohol, povidone, purified talc, sodium lauryl sulphate, sodium starch glycolate, starch, titanium dioxide

Questions or comments?

1-888-577-8033 Monday-Friday 8am-4pm

DG™ health

Compare to the active ingredients of Excedrin® Extra Strength††

READ AND KEEP OUTER CARTON FOR COMPLETE WARNINGS AND PRODUCT INFORMATION

TAMPER EVIDENT: DO NOT USE IF IMPRINTED SAFETY SEAL UNDER CAP IS BROKEN OR MISSING

++ This product is not manufactured or distributed by GSK Consumer Healthcare, distributor of Excedrin® Extra Strength.

DISTRIBUTED BY OLD EAST MAIN CO.
100 MISSION RIDGE
GOODLETTSVILLE, TN 37072

MADE IN INDIA

100%
Satisfaction Guaranteed!
(888) 309-9030